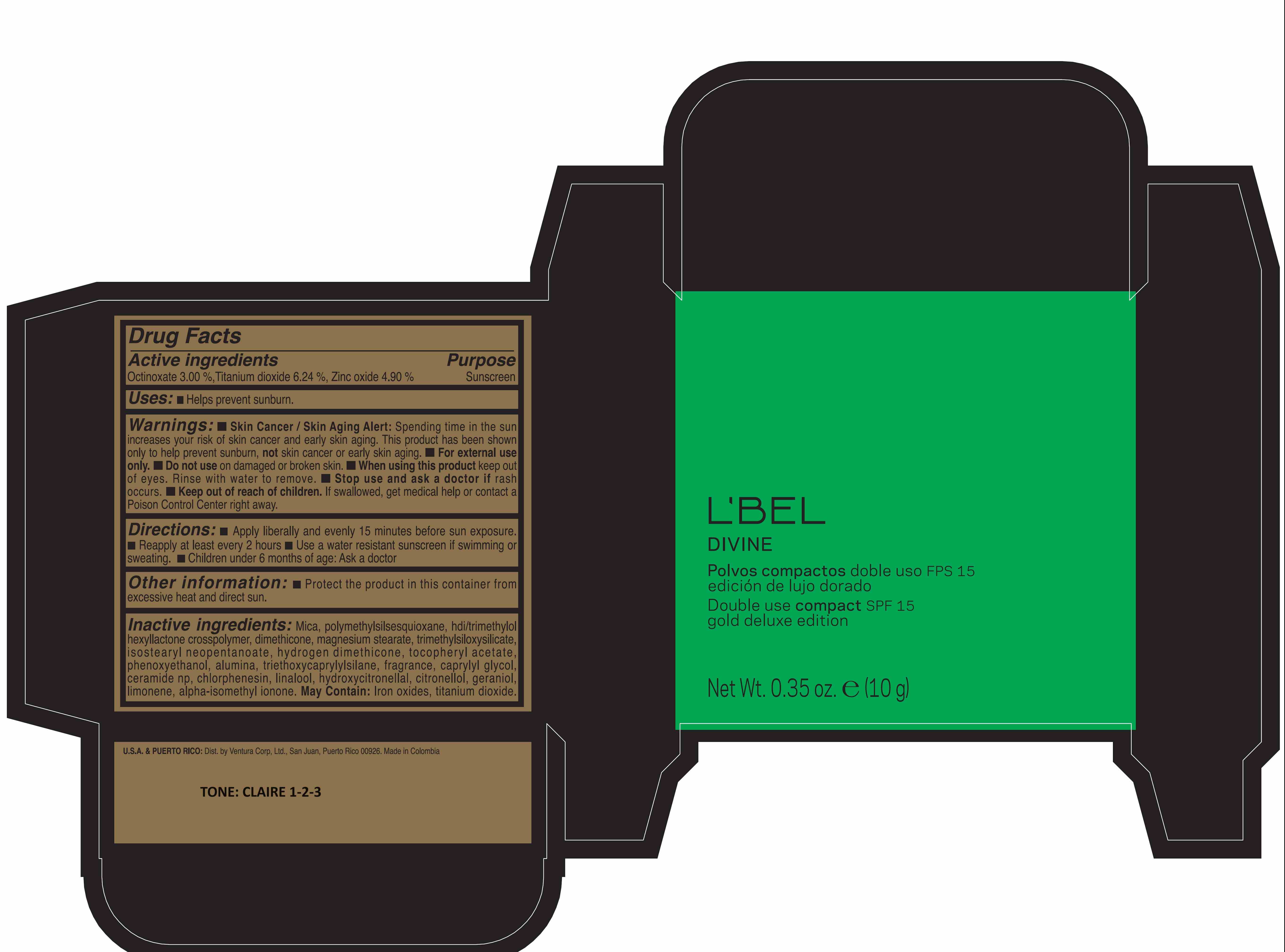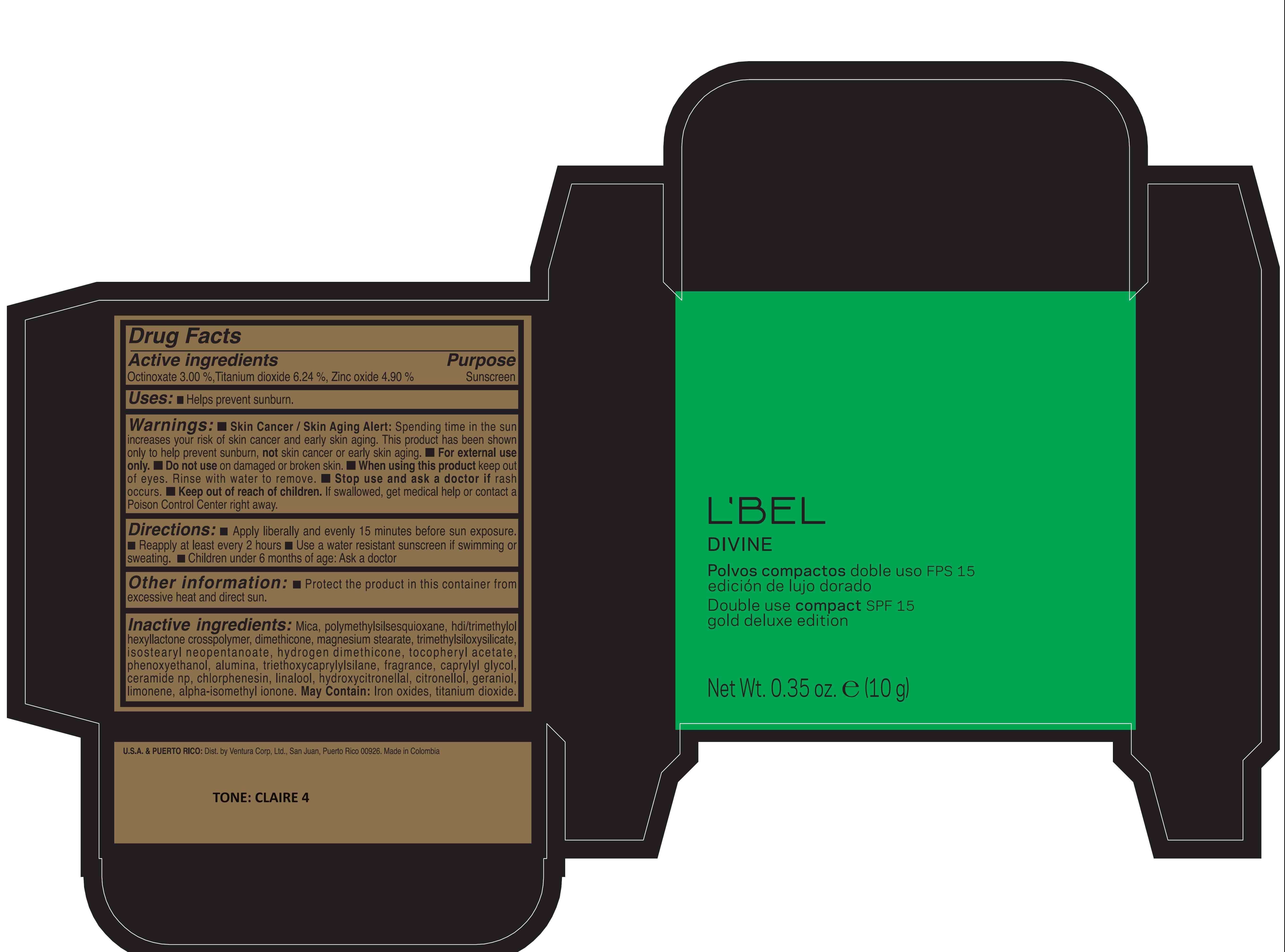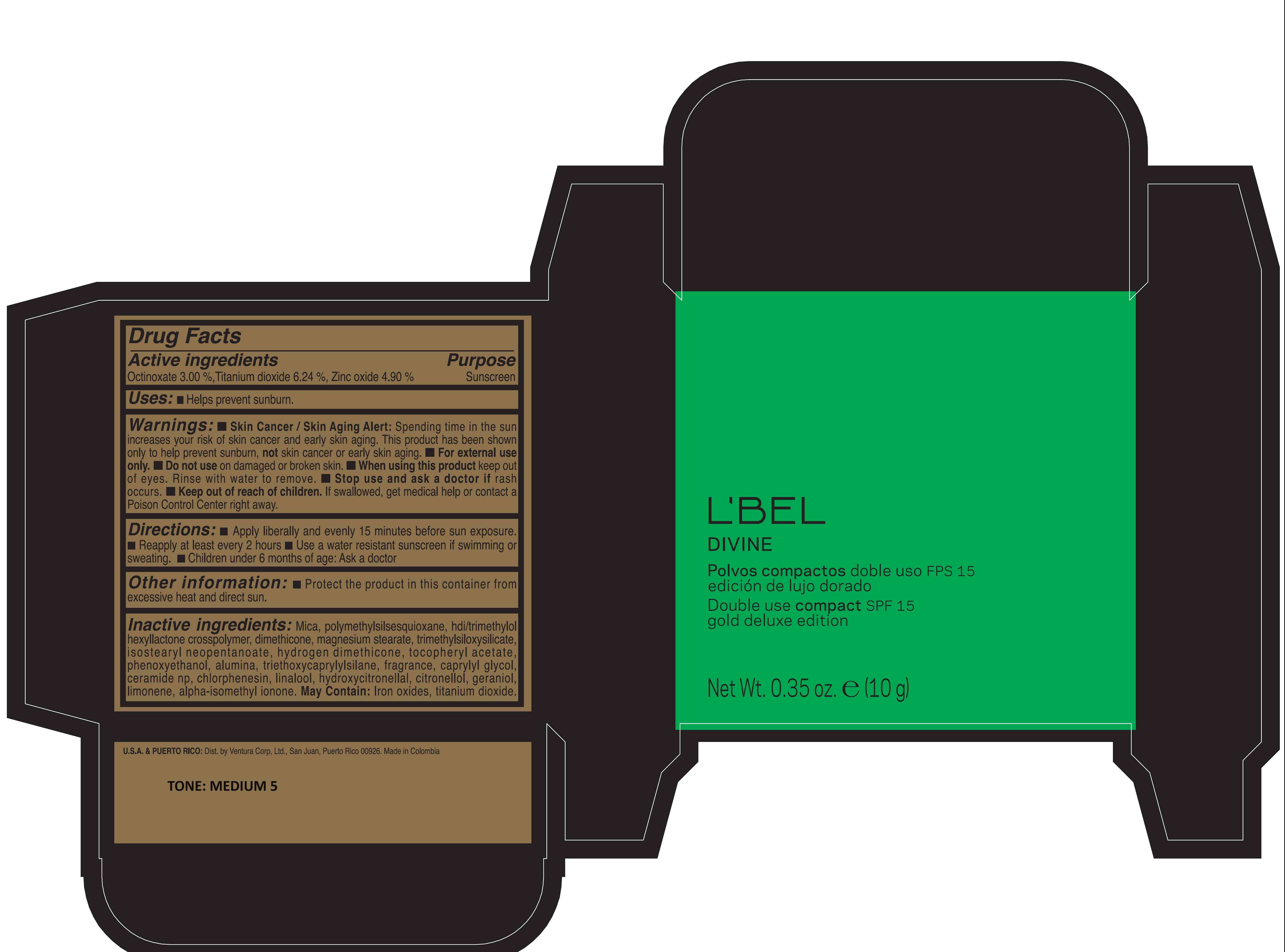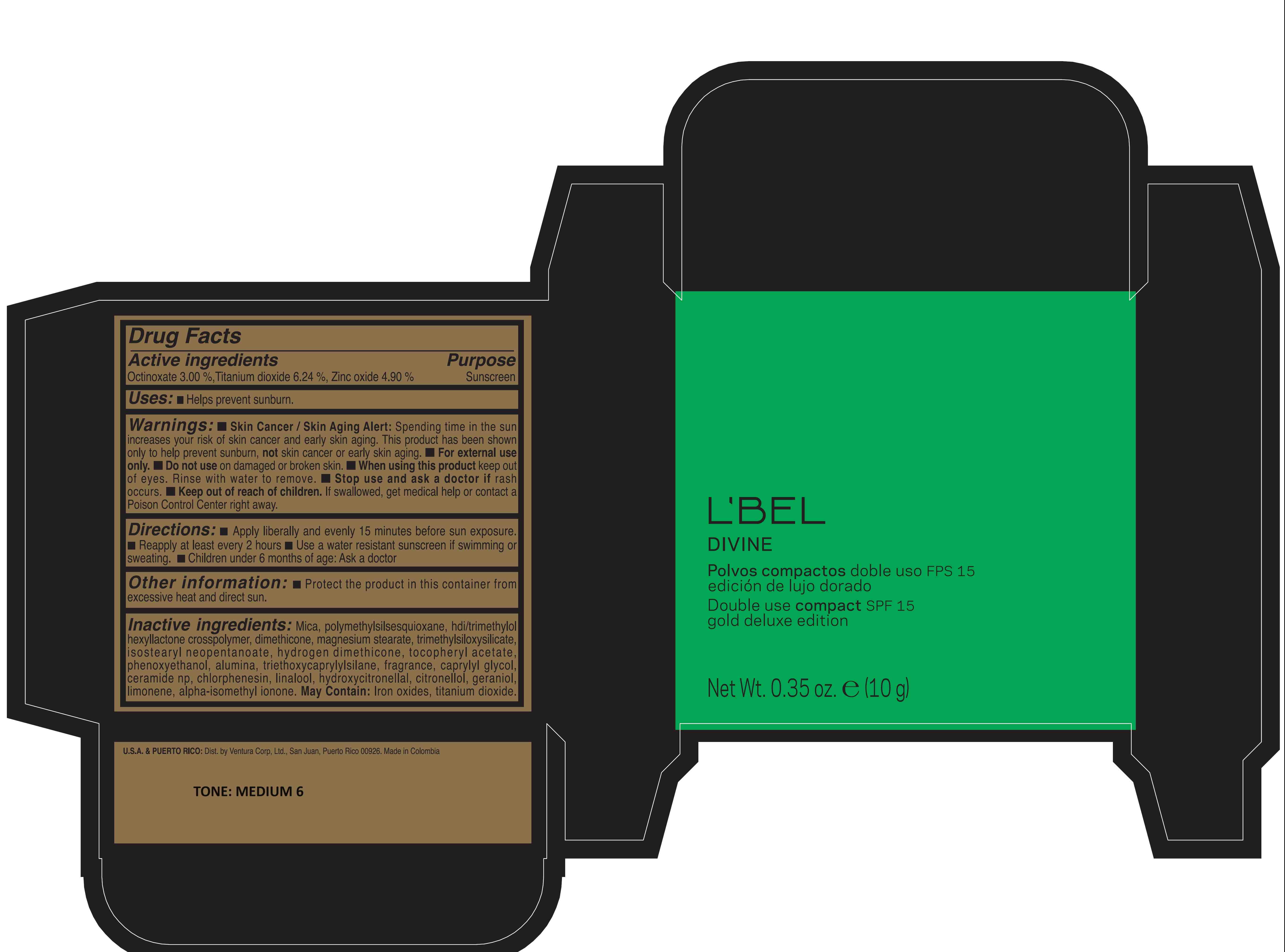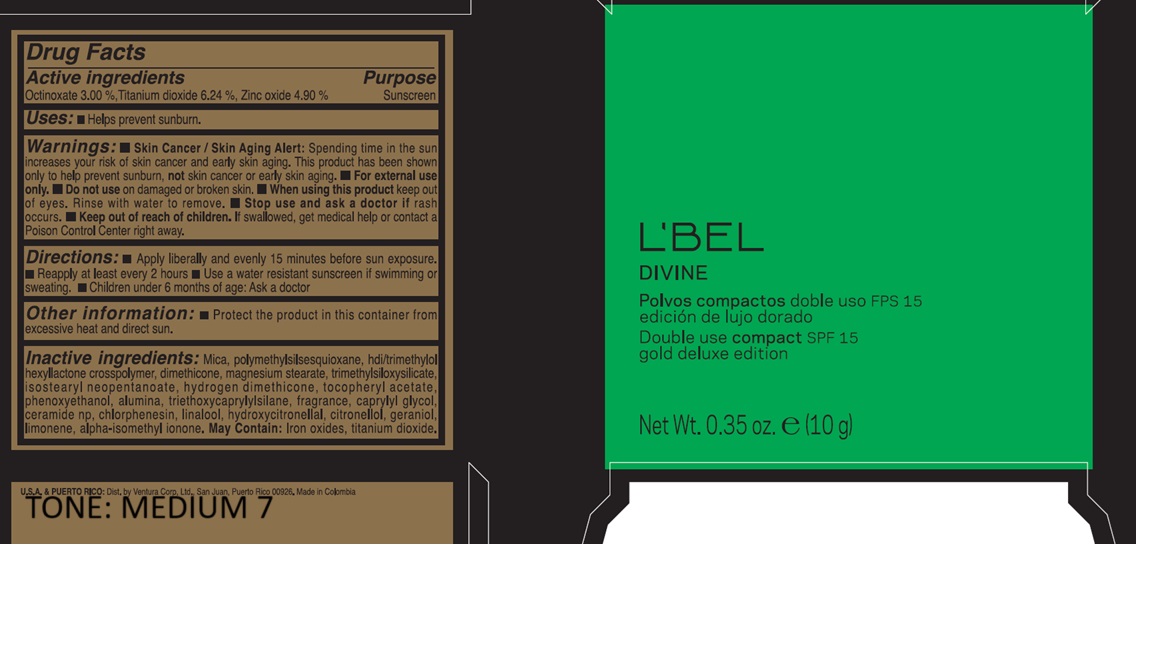 DRUG LABEL: Double Use Compact SPF 15 gold deluxe edition Claire 1-2-3
NDC: 14141-201 | Form: POWDER
Manufacturer: Bel Star S.A. (Colombia)
Category: otc | Type: HUMAN OTC DRUG LABEL
Date: 20250620

ACTIVE INGREDIENTS: ZINC OXIDE 4.9 g/100 g; TITANIUM DIOXIDE 6.24 g/100 g; OCTINOXATE 3 g/100 g
INACTIVE INGREDIENTS: CHLORPHENESIN; ISOMETHYL-.ALPHA.-IONONE; CERAMIDE NP; LINALOOL, (+/-)-; GERANIOL; TRIMETHYLSILOXYSILICATE (M/Q 0.6-0.8); TRIETHOXYCAPRYLYLSILANE; ISOSTEARYL NEOPENTANOATE; PHENOXYETHANOL; CAPRYLYL GLYCOL; .ALPHA.-TOCOPHEROL ACETATE; HEXAMETHYLENE DIISOCYANATE/TRIMETHYLOL HEXYLLACTONE CROSSPOLYMER; FERROSOFERRIC OXIDE; FERRIC OXIDE YELLOW; FERRIC OXIDE RED; POLYMETHYLSILSESQUIOXANE (11 MICRONS); DIMETHICONE; MAGNESIUM STEARATE; HYDROXYCITRONELLAL; MICA; LIMONENE, (+)-; .BETA.-CITRONELLOL, (R)-; HYDROGEN DIMETHICONE (13 CST); ALUMINUM OXIDE

L'BEL DIVINE Double Use Compact SPF 15 gold deluxe edition

Active ingredients Purpose

Octinoxate 3.00% Sunscreen

Titanium Dioxide 6.24% Sunscreen

Zinc Oxide 4.90 % Sunscreen

Uses:

Helps prevent Sunburn

- Keep out of reach of children. If swallowed, get medical help, or contact a Poison Control Center right away.

Stop use and ask a doctor if rash occurs.

WARNINGS

Warnings: Skin Cancer / Skin Aging Alert: Spending time in the sun increases your risk of skin cancer and early skin aging. This product has been shown only to prevent sunburn, not skin cancer or early skin aging.

- For external use only
- Do not use on damaged or broken skin
- When using this product, keep out of eyes. Rinse with water to remove.

Directions:

- Apply liberally and evenly 15 minutes before sun exposure.
- Reapply at least every 2 hours
- Use a water resistant sunscreen if swimming or sweating
- Children under 6 months of age: Ask a doctor

Other information:

- Protect the product in this container from excessive heat and direct sun

INACTIVE INGREDIENT

Inactive ingredients: Mica, polymethylsilsesquioxane, hdi/trimethylol hexyllactone crosspolymer, dimethicone, magnesium stearate, trimethylsiloxysilicate, isostearyl neopentanoate, hydrogen dimethicone, tocopheryl acetate, phenoxyethanol, alumina, triethoxycaprylylsilane, fragrance, caprylyl glycol, ceramide np, chlorphenesin, linalool, hydroxycitronellal, citronellol, geraniol, limonene, alpha-isomethyl ionone, May contain: Iron oxides, titanium dioxide